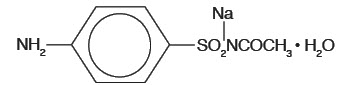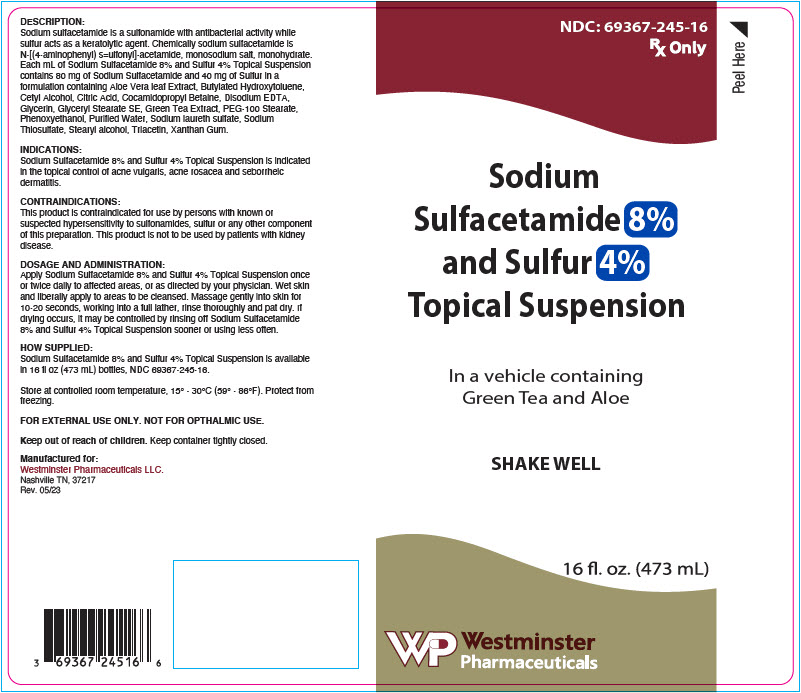 DRUG LABEL: Sodium Sulfacetamide and Sulfur
NDC: 69367-245 | Form: SUSPENSION
Manufacturer: Westminster Pharmaceuticals, LLC
Category: prescription | Type: HUMAN PRESCRIPTION DRUG LABEL
Date: 20250429

ACTIVE INGREDIENTS: SULFACETAMIDE SODIUM 80 mg/1 mL; SULFUR 40 mg/1 mL
INACTIVE INGREDIENTS: ALOE; BUTYLATED HYDROXYTOLUENE; CETYL ALCOHOL; COCAMIDOPROPYL BETAINE; EDETATE DISODIUM; GLYCERIN; GLYCERYL STEARATE SE; GREEN TEA LEAF; PEG-100 STEARATE; WATER; SODIUM THIOSULFATE; STEARYL ALCOHOL; TRIACETIN; XANTHAN GUM; CITRIC ACID MONOHYDRATE; PHENOXYETHANOL; SODIUM LAURETH-3 SULFATE

Sodium Sulfacetamide 8%
and Sulfur 4%
Topical Suspension

In a vehicle containing Green Tea and Aloe

Rx Only

FOR EXTERNAL USE ONLY. NOT FOR OPHTHALMIC USE.

DESCRIPTION

Sodium sulfacetamide is a sulfonamide with antibacterial activity while sulfur acts as a keratolytic agent. Chemically sodium sulfacetamide is N-[(4-aminophenyl) sulfonyl]-acetamide, monosodium salt, monohydrate.

The structural formula is:

Each mL of Sodium Sulfacetamide 8% and Sulfur 4% Topical Suspension contains 80 mg of Sodium Sulfacetamide and 40 mg of Sulfur in a formulation containing Aloe Vera leaf Extract, Butylated Hydroxytoluene, Cetyl Alcohol, Citric Acid, Cocamidopropyl Betaine, Disodium EDTA, Glycerin, Glyceryl Stearate SE, Green Tea Extract, PEG-100 Stearate, Phenoxyethanol, Purified Water, Sodium laureth sulfate, Sodium Thiosulfate, Stearyl alcohol, Triacetin, Xanthan Gum.

CLINICAL PHARMACOLOGY

The most widely accepted mechanism of action of sulfonamides is the Woods-Fildes theory, which is based on the fact that sulfonamides act as competitive antagonists to para-aminobenzoic acid (PABA), an essential component for bacterial growth. While absorption through intact skin has not been determined, sodium sulfacetamide is readily absorbed from the gastrointestinal tract when taken orally and excreted in the urine, largely unchanged. The biological half-life has variously been reported as 7 to 12.8 hours. The exact mode of action of sulfur in the treatment of acne is not known, but it has been reported that it inhibits the growth of Propionibacterium acnes and the formation of free fatty acids.

INDICATIONS

Sodium Sulfacetamide 8% and Sulfur 4% Topical Suspension is indicated in the topical control of acne vulgaris, acne rosacea and seborrheic dermatitis.

CONTRAINDICATIONS

This product is contraindicated for use by persons with known or suspected hypersensitivity to sulfonamides, sulfur or any other component of this preparation. This product is not to be used by patients with kidney disease.

WARNINGS

Although rare, sensitivity to sodium sulfacetaminde may occur. Therefore, caution and careful supervision should be observed when prescribing this drug for patients who may be prone to hypersensitivity to topical sulfonamides. Systemic toxic reactions such as agranulocytosis, acute hemolytic anemia, purpura hemorrhagica, drug fever, jaundice and contact dermatitis indicate hypersensitivity to sulfonamides. Particular caution should be employed if areas of denuded or abraded skin are involved.

FOR EXTERNAL USE ONLY. Keep away from eyes. Keep out of reach of children. Keep container tightly closed.

PRECAUTIONS

General

If irritation develops, use of the product should be discontinued and appropriate therapy instituted. Patients should be carefully observed for possible local irritation or sensitization during longterm therapy. The object of this therapy is to achieve desquamation without irritation, but sodium sulfacetamide and sulfur can cause reddening and scaling of the epidermis. These side effects are not unusual in the treatment of acne vulgaris, but patients should be cautioned about the possibilty.

Information for patients

Avoid contact with eyes, eyelids, lips and mucous membranes. If accidental contact occurs, rinse with water. If excessive irritation develops, discontinue use and consult your physician.

Carcinogenesis, Mutagenesis and Impairment of Fertility

Long-term studies in animals have not been performed to evaluate carcinogenic potential.

PREGNANCY

Category C

Animal reproduction studies have not been conducted with Sodium Sulfacetamide 8% and Sulfur 4% Topical Suspension. It is not known whether Sodium Sulfacetamide 8% and Sulfur 4% Topical Suspension can cause fetal harm when administered to a pregnant woman or can affect reproduction capacity. Sodium Sulfacetamide 8% and Sulfur 4% Topical Suspension should be given to a pregnant woman only if clearly needed.

NURSING MOTHERS

It is not known whether sodium sulfacetamide is excreted in the human milk following topical use of Sodium Sulfacetamide 8% and Sulfur 4% Topical Suspension. However, small amounts of orally administered sulfonamides have been reported to be eliminated in human milk. In view of this and because many drugs are excreted in human milk, caution should be exercised when Sodium Sulfacetamide 8% and Sulfur 4% Topical Suspension is administered to a nursing woman.

PEDIATRIC USE

Safety and effectiveness in children under the age of 12 have not been established.

ADVERSE REACTIONS

Although rare, sodium sulfacetamide may cause local irritation.

Call your doctor for medical advice about side effects. To report a serious adverse event, please contact Westminster Pharmaceuticals at 1-844-221-7294.

OVERDOSAGE

The oral LD50 of sulfacetamide in mice is 16.5 g/kg. In the event of overdosage, emergency treatment should be started immediately.

Manifestations

Overdosage may cause nausea and vomiting. Large oral overdosage may cause hematuria, crystalluria and renal shutdown due to the precipitation of sulfa crystals in the renal tubules and the urinary tract. For treatment, contact your local Poison Control Center (1-800-222-1222), or your doctor.

DOSAGE AND ADMINISTRATION

Apply Sodium Sulfacetamide 8% and Sulfur 4% Topical Suspension once or twice daily to affected areas, or as directed by your physician. Wet skin and liberally apply to areas to be cleansed. Massage gently into skin for 10-20 seconds, working into a full lather, rinse thoroughly and pat dry. If drying occurs, it may be controlled by rinsing off Sodium Sulfacetamide 8% and Sulfur 4% Topical Suspension sooner or using less often.

HOW SUPPLIED

Sodium Sulfacetamide 8% and Sulfur 4% Topical Suspension is available in 16 fl oz (473 mL) bottles, NDC 69367-245-16.

STORAGE AND HANDLING

Store at controlled room temperature, 15° - 30°C (59° - 86°F). Protect from freezing.

KEEP THIS AND ALL MEDICATIONS OUT OF THE REACH OF CHILDREN.

All prescription substitutions using this product shall be made subject to state and federal statutes as applicable. NOTE: this is not an Orange Book product and has not been subjected to FDA therapeutic equivalency or other equivalency testing. No representation is made as to generic status or bioequivalency. Each person recommending a prescription substitution using this product shall make such recommendations based on each such person's professional opinion and knowledge, upon evaluating the active ingredients, excipients, inactive ingredients and chemical formulation information provided herein.

Manufactured for:
Westminster Pharmaceuticals LLC
Nashville TN, 37217
Rev. 05/23

PRINCIPAL DISPLAY PANEL - 473 mL Bottle Label

NDC: 69367-245-16
Rx Only

Peel Here

Sodium
Sulfacetamide 8%
and Sulfur 4%
Topical Suspension

In a vehicle containing
Green Tea and Aloe

SHAKE WELL

16 fl. oz. (473 mL)

Westminster
Pharmaceuticals